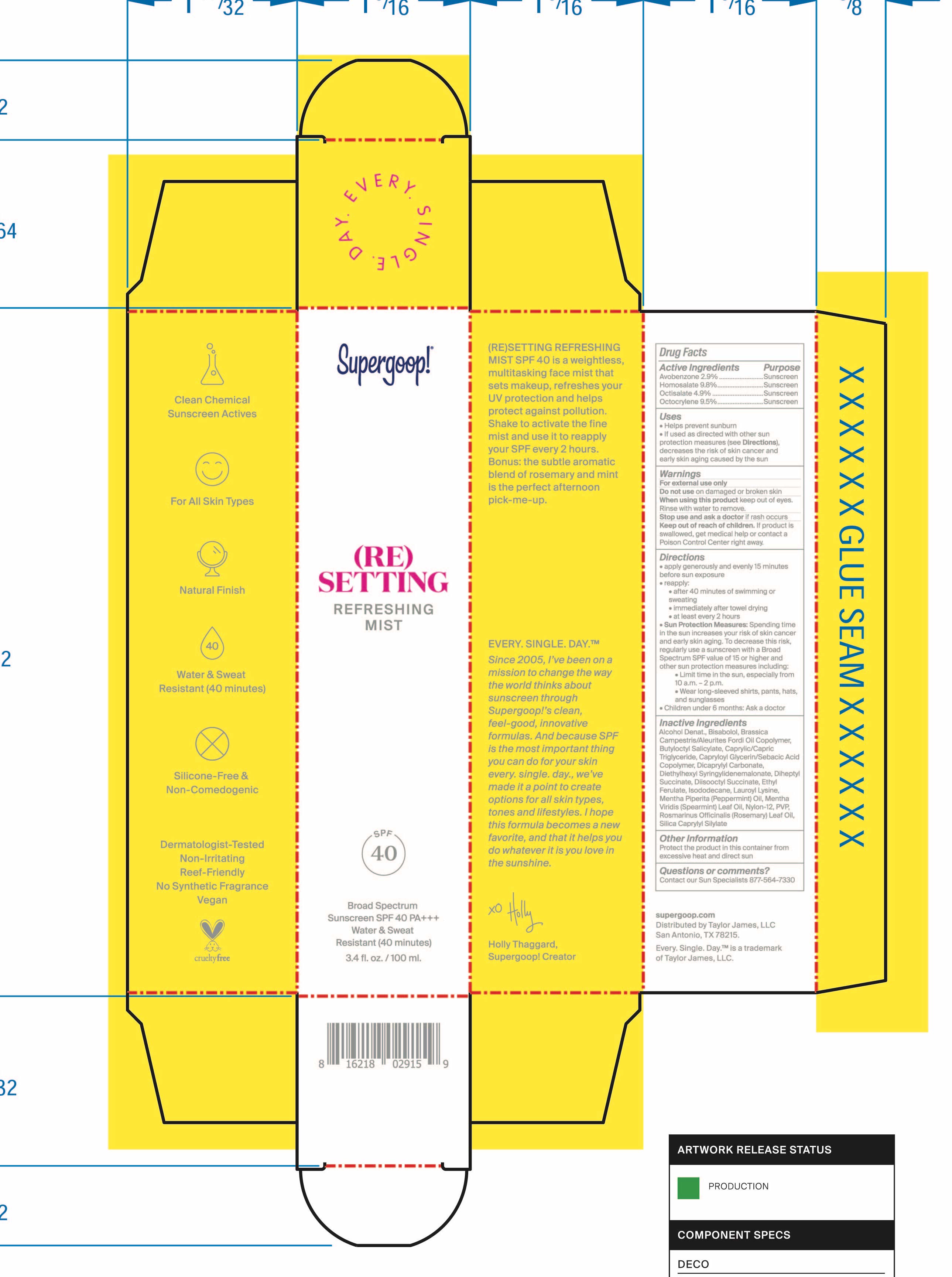 DRUG LABEL: (Re)Setting Refreshing Mist SPF 40
NDC: 75936-361 | Form: SPRAY
Manufacturer: Supergoop, LLC
Category: otc | Type: HUMAN OTC DRUG LABEL
Date: 20241205

ACTIVE INGREDIENTS: AVOBENZONE 2.9 g/100 mL; HOMOSALATE 9.8 g/100 mL; OCTOCRYLENE 9.5 g/100 mL; OCTISALATE 4.9 g/100 mL
INACTIVE INGREDIENTS: ALCOHOL; DIHEPTYL SUCCINATE; LEVOMENOL; BUTYLOCTYL SALICYLATE; ETHYL FERULATE; LAUROYL LYSINE; DIETHYLHEXYL SYRINGYLIDENEMALONATE; SPEARMINT OIL; ROSEMARY OIL; NYLON-12; MEDIUM-CHAIN TRIGLYCERIDES; POVIDONE, UNSPECIFIED; PEPPERMINT OIL; CAPRYLOYL GLYCERIN/SEBACIC ACID COPOLYMER (2000 MPA.S); DICAPRYLYL CARBONATE; ISODODECANE

(Re)Setting Refreshing Mist SPF 40

Active ingredients Purpose

Avobenzone 2.9% Sunscreen

Homosalate 9.8% Sunscreen

Octisalate 4.9% Sunscreen

Octocrylene 9.5% Sunscreen

PURPOSE

- Helps Prevent Sunburn
- If used as directed with other sun protection measures (see Directions), decreases the risk of skin cancer and early skin aging caused by the sun

Keep out of reach of children

If product is swallowed, get medical help or contact a poison Control Center right away

Stop use and ask a doctor if rash occurs

WARNINGS

For external use only
Do not use on damaged or broken skin
When using this product keep out of eyes. Rinse with water to remove.

DOSAGE AND ADMINISTRATION

- Apply generously and evenly 15 minutes before sun exposure

- reapply:
- after 40 minutes of swimming or sweating
- immediately after towel drying
- at least every 2 hours.
- Sun Protection Measures Spending time in the sun increases your risk of

skin cancer and early skin aging. To decrease this risk, regularly use a
sunscreen with a Broad-Spectrum SPF value of 15 or higher and other sun
protection measures including:

• limit your time in the sun, especially from 10
a.m. – 2 p.m.

• wear long-sleeved shirts, pants, hats, and sunglasses

•Children under 6 months of age: ask a doctor.

Inactive ingredients:

Alcohol Denat., Bisabolol, Brassica Camprestris/Aleurites Fordi Oil Copolymer, Butyloctyl Salicylate, Caprylic/Capric Triglyceride, Capryloyl Glycerin/Sebacic Acid Copolymer, Dicaprylyl Carbonate, Diethylhexyl Syringylidenemalonate, Diheptyl Succinate, Diisooctyl Succinate, Ethyl Ferulate, Isododecane, Lauroyl Lysine, Mentha Piperita (Peppermint) Oil, Mentha Viridis (Spearmint) Leaf Oil, Nylon-12, PVP, Rosemarinus Officinalis (Rosemary) Leaf Oil, Silica Caprylyl Silylate

PACKAGE LABEL

Supergoop!

(Re) Setting Refreshing Mist

SPF 40

Broad Spectrum

Sunscreen SPF 40 PA+++

Water & Sweat Resistant (40 minutes)

3.4 fl. oz. / 100 ml.